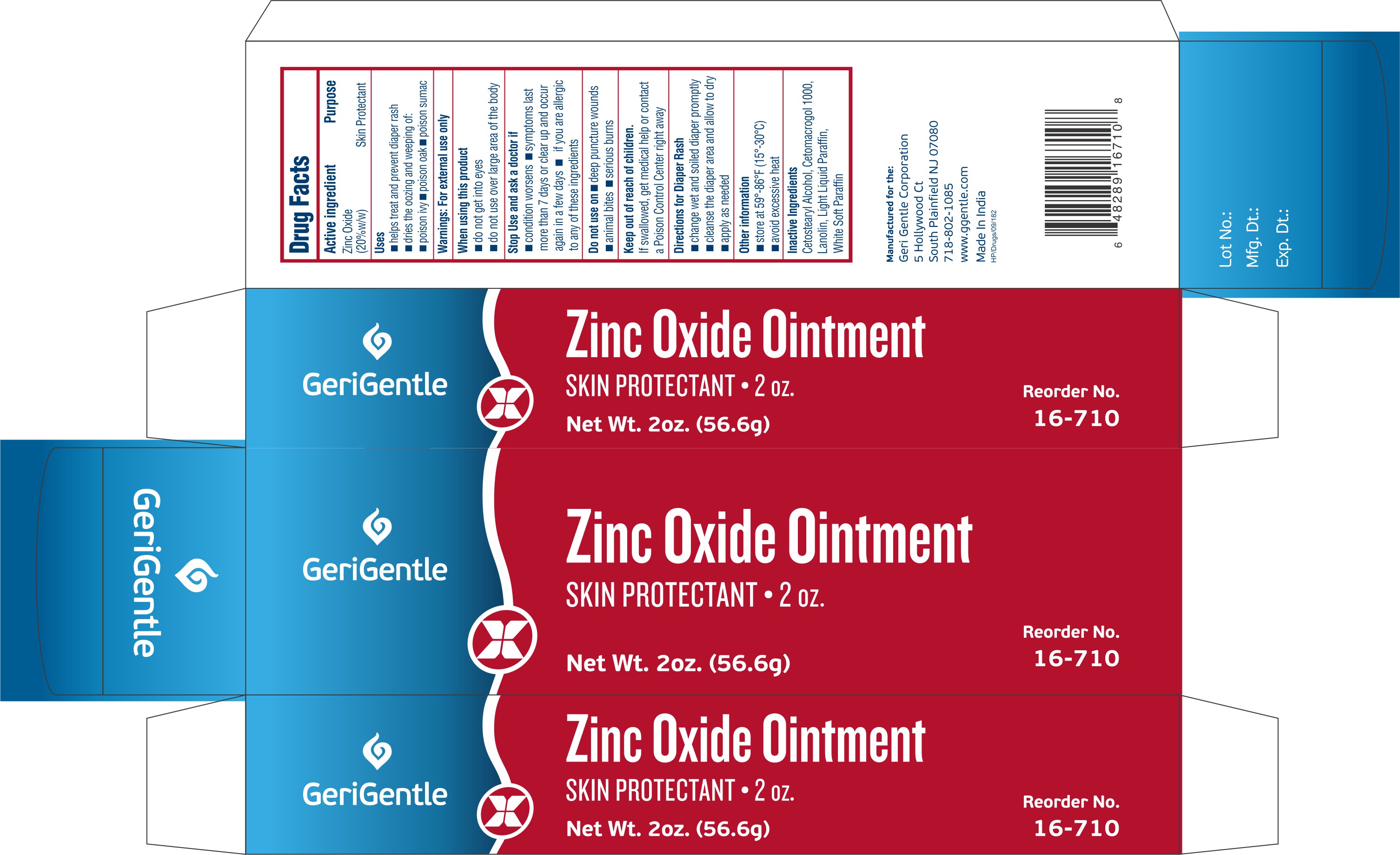 DRUG LABEL: Zinc Oxide
NDC: 69771-109 | Form: OINTMENT
Manufacturer: Geri-Gentle Corporation
Category: otc | Type: HUMAN OTC DRUG LABEL
Date: 20250929

ACTIVE INGREDIENTS: ZINC OXIDE 20 g/100 g
INACTIVE INGREDIENTS: LANOLIN; CETOSTEARYL ALCOHOL; CETETH-20; LIGHT MINERAL OIL; PETROLATUM

Zinc Oxide

Drug Facts

Active ingredient

Zinc Oxide (20%w/w)

Purpose

Skin Protectant

Uses

- helps treat and prevent diaper rash
- dries the oozing and weeping of:
  - poison ivy
  - poison oak
  - poison sumac

Warnings

For external use only

When using this product

- do not get into eyes
- do not use over large area of the body

Stop Use and ask a doctor if

- condition worsens
- symptoms last more than 7 days or clear up and occur again in a few days
- if you are allergic to any of these ingredients

Do not use on

- deep puncture wounds
- animal bites
- serious burns

Keep out of reach of children.

If swallowed, get medical help or contact a Poison Control Center right away

Directions for Diaper Rash

- change wet and soiled diaper promptly
- cleanse the diaper area and allow to dry
- apply as needed

Other information

- store at 59°-86°F (15°-30°C)
- avoid excessive heat

Inactive Ingredients

Cetostearyl Alcohol, Cetomacrogol 1000, Lanolin, Light Liquid Paraffin, White Soft Paraffin